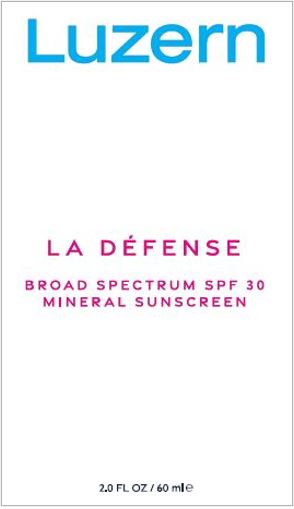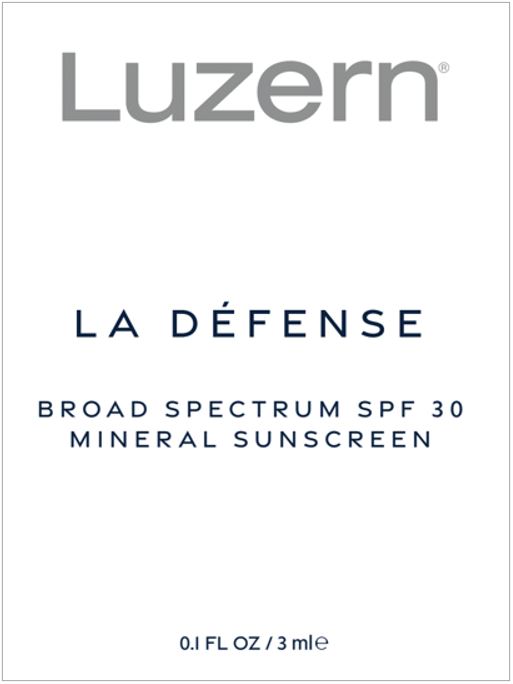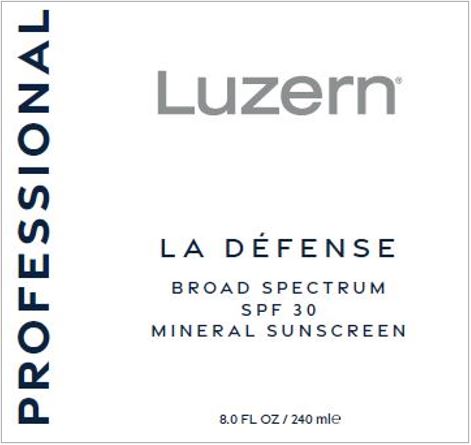 DRUG LABEL: La Defense Broad Spectrum SPF 30 Mineral Sunscreen
NDC: 63127-101 | Form: LOTION
Manufacturer: Luzern Laboratories, Inc
Category: otc | Type: HUMAN OTC DRUG LABEL
Date: 20250721

ACTIVE INGREDIENTS: ZINC OXIDE 15 g/100 mL; TITANIUM DIOXIDE 3.57 g/100 mL
INACTIVE INGREDIENTS: ARGAN OIL; LEVOMENOL; BUDDLEJA DAVIDII LEAF; C12-20 ALKYL GLUCOSIDE; C14-22 ALCOHOLS; GREEN TEA LEAF; CAPRYLHYDROXAMIC ACID; MEDIUM-CHAIN TRIGLYCERIDES; CARBOMER HOMOPOLYMER, UNSPECIFIED TYPE; CETYL ALCOHOL; CHONDRUS CRISPUS CARRAGEENAN; CITRIC ACID MONOHYDRATE; ETHYL MACADAMIATE; ETHYLHEXYL ISONONANOATE; ETHYLHEXYLGLYCERIN; GLYCERIN; GLYCERYL MONOCAPRYLATE; GLYCERYL ISOSTEARATE; GLYCERYL 1-UNDECYLENATE; GLYCYRRHIZA GLABRA; SUNFLOWER OIL; HEXYLDECANOL; ISOSTEARYL PALMITATE; ARGININE; LEONTOPODIUM NIVALE SUBSP. ALPINUM FLOWERING TOP; LEVULINIC ACID; METHYLPROPANEDIOL; OCTYLDODECYL NEOPENTANOATE; PANTHENOL; POLYHYDROXYSTEARIC ACID STEARATE; PROPANEDIOL; SODIUM ASCORBYL PHOSPHATE; HYALURONATE SODIUM; SODIUM LEVULINATE; SODIUM PYRROLIDONE CARBOXYLATE; STEARETH-2; STEARETH-21; THYME; TOCOPHEROL; TOCOPHERSOLAN; .ALPHA.-TOCOPHEROL ACETATE; WATER; GINGER

La Défense Broad Spectrum SPF 30 Mineral Sunscreen

Active Ingredients:

Zinc Oxide (CI 77947) 15%
Titanium Dioxide 3.57%

Purpose

Sunscreen

Uses:

Helps prevent sunburn

Warnings:

For external use only
Avoid contact with eyes.If contact occurs, rinse thoroughly with water. Do not useon damaged or broken skin. Discontinue use if skin irritation developsor increases. If irritation persists, consult a health care practitioner. If swallowed, get medical help or contact a Poison Control Center right away.

Keep out of reach of children.

Consult a health care practitioner prior to use on children less than six months of age.

Directions

Apply liberally/generously (and evenly) 15 minutes before sun exposure; Reapply at least every 2 hours or after swimming, towel drying, perspiring heavily and washing; and for use on children less than 6 months of age, consult a health care practitioner.
Sun Protection Measures:
Spending time in the sun increases your risk of skin cancer and early skin aging. To decrease this risk, regularly use a sunscreen with a Broad Spectrum SPF value of 15 or higher and other measures including:

- Limit time in the sun, especially from 10am – 2pm.
- Wear Long-sleeved shirts, pants, hats and sunglasses.
- Reapply after 40 minutes of swimming or sweating.
- Reapply immediately after towel drying.

Inactive Ingredients:

ARGANIA SPINOSA (ARGAN) KERNEL OIL, BISABOLOL, BUDDLEJA DAVIDII LEAF EXTRACT, C1220 ALKYL GLUCOSIDE, C1422 ALCOHOLS, CAMELLIA SINENSIS (GREEN TEA) LEAF EXTRACT, CAPRYLHYDROXAMIC ACID, CAPRYLIC/CAPRIC TRIGLYCERIDE, CARBOMER, CETYL ALCOHOL, CHONDRUS CRISPUS EXTRACT, CITRIC ACID, ETHYL MACADAMIATE, ETHYLHEXYL ISONONANOATE, ETHYLHEXYLGLYCERIN, FRAGRANCE (PARFUM), GLYCERIN, GLYCERYL CAPRYLATE , GLYCERYL ISOSTEARATE, GLYCERYL UNDECYLENATE, GLYCYRRHIZA GLABRA (LICORICE) ROOT EXTRACT, HELIANTHUS ANNUUS (SUNFLOWER) SEED OIL, HEXYLDECANOL, ISOSTEARYL PALMITATE, JOJOBA ESTERS, L-ARGININE, LEONTOPODIUM ALPINUM (EDELWEISS) FLOWER/LEAF EXTRACT, LEVULINIC ACID, METHYLPROPANEDIOL, OCTYLDODECYL NEOPENTANOATE, PANTHENOL, POLYHYDROXYSTEARIC ACID, PROPANEDIOL, SODIUM ASCORBYL PHOSPHATE, SODIUM HYALURONATE, SODIUM LEVULINATE, SODIUM PCA, STEARETH-2, STEARETH-21, TETRASODIUM GLUTAMATE DIACETATE, THYMUS VULGARIS (THYME) FLOWER/LEAF EXTRACT, TOCOPHEROL, TOCOPHERSOLAN, TOCOPHERYL ACETATE, WATER (AQUA), ZINGIBER OFFICINALE (GINGER) ROOT EXTRACT.

Other information

Protect the product in this container from excessive heat and direct sunlight.
Comments and Questions:
1-888-591-7800

Principal Display Panel – 60 mL Tube Label

LUZERN

LA DÉFENSE
BROAD SPECTRUM SPF 30
MINERAL SUNSCREEN

2.0 FL OZ / 60 ml℮

Manufactured for and dist. by/Fabriqué pour et distribué par
Luzern Laboratories, Inc
50 Washington Street, Norwalk, CT 06854 / Biorius / UK: Shelton Street 71-
London WC2H9JQ, Great-Britain / EU: Rue Wauters 113-7170 Manage, Belgium

Principal Display Panel – 3 mL Tube Label

LUZERN®

LA DÉFENSE
BROAD SPECTRUM SPF 30
MINERAL SUNSCREEN

0.1 FL OZ / 3 ml℮

Manufactured for and dist. by/Fabriqué pour et distribué par Luzern Laboratories, Inc
50 Washington Street, Norwalk, CT 06854 / Biorius / UK: Shelton Street 71-
London WC2H9JQ, Great-Britain / EU: Rue Wauters 113-7170 Manage, Belgium

Principal Display Panel – 240 mL Bottle Label

PROFESSIONAL

LUZERN®

LA DÉFENSE
BROAD SPECTRUM
SPF 30
MINERAL SUNSCREEN

8.0 FL OZ / 240 ml℮

Manufactured for and dist. by/Fabriqué pour et distribué par Luzern Laboratories, Inc
50 Washington Street, Norwalk, CT 06854 / Biorius / UK: Shelton Street 71-
London WC2H9JQ, Great-Britain / EU: Rue Wauters 113-7170 Manage, Belgium